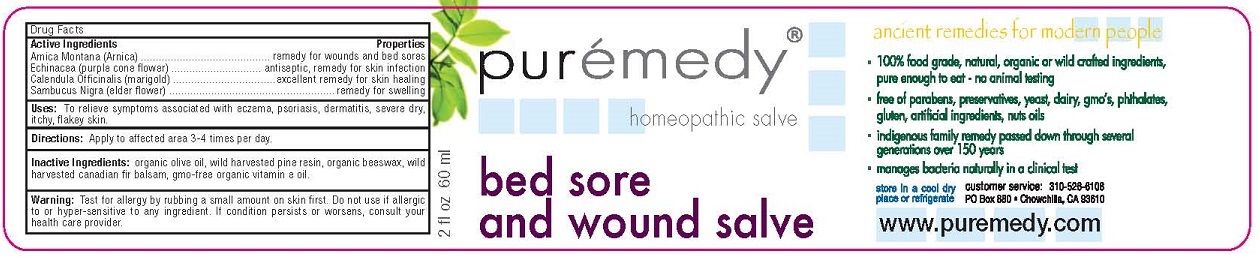 DRUG LABEL: BED SORE AND WOUND
NDC: 52810-207 | Form: SALVE
Manufacturer: PUREMEDY
Category: homeopathic | Type: HUMAN OTC DRUG LABEL
Date: 20240111

ACTIVE INGREDIENTS: ARNICA MONTANA 2 [hp_X]/100 mL; ECHINACEA PURPUREA 2 [hp_X]/100 mL; CALENDULA OFFICINALIS FLOWER 2 [hp_X]/100 mL; SAMBUCUS NIGRA FLOWER 1 [hp_X]/100 mL
INACTIVE INGREDIENTS: OLIVE OIL; PINE NEEDLE OIL (PINUS SYLVESTRIS); YELLOW WAX; ABIES BALSAMEA LEAF OIL; TOCOPHEROL

BED SORE AND WOUND SALVE (52810-207)

ACTIVE INGREDIENTS

ARNICA MONTANA (ARNICA)

ECHINACEA (PURPLE CONEFLOWER)

CALENDULA OFFICINALIS (MARIGOLD)

SAMBUCUS NIGRA (ELDER FLOWER)

PROPERTIES

REMEDY FOR WOUNDS AND BED SORES

ANTISEPTIC, REMEDY FOR SKIN INFECTION

EXCELLENT REMEDY FOR SKIN HEALING

REMEDY FOR SWELLING

USES

TO RELIEVE SYMPTOMS ASSOCIATED WITH ECZEMA, PSORIASIS, DERMATITIS, SEVIERE DRY, ITCHY FLAKY SKIN

DIRECTIONS

APPLY TO AFFECTED AREA 3-4 TIMES PER DAY.

INACTIVE INGREDIENTS

ORGANIC OLIVE OIL, WILD HARVESTED PINE RESIN, ORGANIC BEESWAX, WILD HARVESTED CANADIAN FIR BALSAM, GMO-FREE ORGANIC VITAMIN E OIL.

WARNING

TEST FOR ALLERGY BY RUBBING A SMALL AMOUNT ON SKIN FIRST. DO NOT USE IF ALLERGIC TO OR HYPER-SENSITIVE TO ANY INGREDIENT. IF CONDITION PERSISTS OR WORSENS, CONSULT YOUR HEALTH CARE PROVIDER.

KEEP OUT OF REACH OF CHILDREN.

OTHER SAFETY INFORMATION

STORE IN A COOL DRY PLACE OR REFRIGERATE